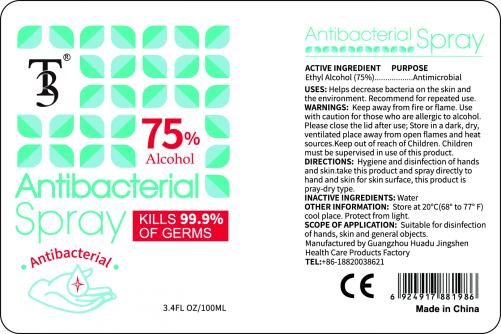 DRUG LABEL: not have
NDC: 74996-011 | Form: SPRAY
Manufacturer: Guangzhou huadu jingshen health care products factory
Category: otc | Type: HUMAN OTC DRUG LABEL
Date: 20200505

ACTIVE INGREDIENTS: ALCOHOL 75 mL/100 mL
INACTIVE INGREDIENTS: WATER

Antibacterial Spray

ACTIVE INGREDIENT

Ethyl Alcohol(75%)

PURPOSE

Antimicrobial

USES

Helps decrease bacteria on the skin and the environment.Recommend for repeated use.

WARNINGS

Keep away from fire or flame.Use with caution for those who are allergic to alcohol.

Please close the lid after use;Store in a dark, dry,ventilated place away from open flames and heat

sources.Keep out of reach of Children.Children must be supervised in use of this product.

DIRECTIONS

Hygiene and disinfection of hands and skin.take this product and spray directly to hand and skin for skin surface, this product is

pray-dry type.

OTHER INFORMATION

Store at 20℃(68° to 77° F) cool place.Protect from light.

INACTIVE INGREDIENTS

Water